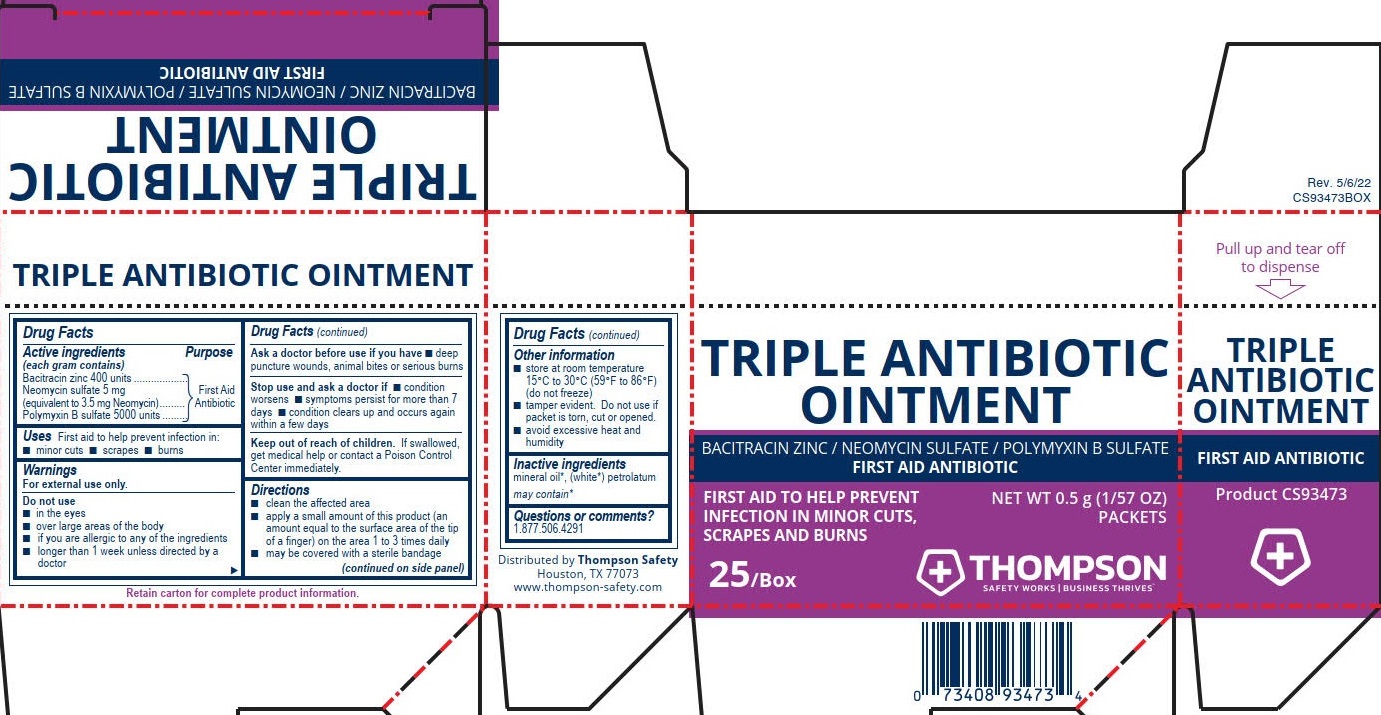 DRUG LABEL: Thompson Triple Antibiotic
NDC: 73408-935 | Form: OINTMENT
Manufacturer: Thompson
Category: otc | Type: HUMAN OTC DRUG LABEL
Date: 20250908

ACTIVE INGREDIENTS: POLYMYXIN B SULFATE 5000 [USP'U]/1 g; BACITRACIN ZINC 400 [USP'U]/1 g; NEOMYCIN SULFATE 3.5 mg/1 g
INACTIVE INGREDIENTS: WHITE PETROLATUM

Thompson Triple Antibiotic

Active ingredients

(each gram contains)

Bacitracin Zinc 400 units

Neomycin Sulfate 5 mg

(equivalent to 3.5 mg Neomycin)

Polymyxin B Sulfate 5000 units

Purpose

First Aid Antibiotic

First Aid Antibiotic

First Aid Antibiotic

Uses

First aid to help prevent infection in:

- minor cuts
- scrapes
- burns

Warnings

For external use only.

Do not use

- in the eyes
- over large areas of the body
- if you are allergic to any of the ingredients
- longer than 1 week unless directed by a doctor

Ask a doctor before use if you have

- deep puncture wounds, animal bites, or serious burns

Stop use and ask a doctor if

- condition worsens
- symptoms persist for more than 7 days
- Condition clears up and occurs again within a few days

Keep out of reach of children. If swallowed, get medical help or contact a Poison Control Center immediately.

Directions

- Clean the affected area
- Apply a small amount of this product (an amount equal to the surface area of the tip of a finger) on the area 1 to 3 times daily
- May be covered with a sterile bandage

Other information

- store at room temperature 15ºC to 30ºC (56ºF to 86ºF) (do not freeze)
- tamper evident. Do not use if packet is torn, cut or opened
- avoid excesive heat and humidity

Inactive ingredients

mineral oil*, (white*) petrolatum

may contain*

Questions or comments? 1.877.506.4291

PACKAGE LABEL

Thompson

Triple Antibiotic Ointment

Bacitracin Zinc/ Neomycin Sulfate/ Polymyxin B Sulfate

First Aid Antibiotic

First Aid to Help Prevent Infection, in Minor Cuts, Scrapes and Burns

Net WT 0.5 g (1/57 OZ) Packets

25/Box

Thompson

Safety Works | Business Thrives™